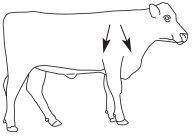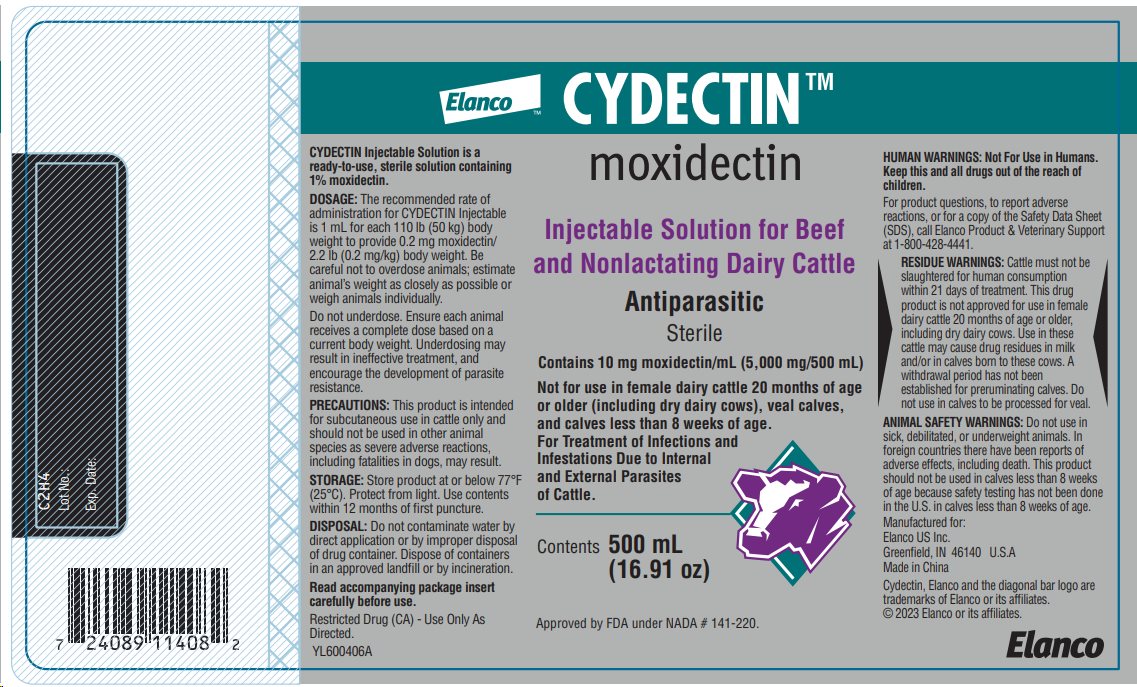 DRUG LABEL: Cydectin
NDC: 58198-0028 | Form: INJECTION, SOLUTION
Manufacturer: Elanco US Inc.
Category: animal | Type: OTC ANIMAL DRUG LABEL
Date: 20250124

ACTIVE INGREDIENTS: moxidectin 10 mg/1 mL

Approved by FDA under NADA # 141-220.

CYDECTINTM

moxidectin

Injectable Solution for Beef and Nonlactating Dairy Cattle

Antiparasitic

Contains 10 mg moxidectin/mL

Not for use in female dairy cattle 20 months of age or older (including dry dairy cows), veal calves, and calves less than 8 weeks of age.

For Treatment of Infections and Infestations Due to Internal and External Parasites of Cattle

Consult your veterinarian for assistance in the diagnosis, treatment and control of parasitism.

PRODUCT DESCRIPTION

CYDECTIN Injectable Solution is a ready-to-use, sterile solution containing 1% moxidectin. Moxidectin is an endectocide in the milbemycin chemical class which shares the distinctive mode of action characteristic of macrocyclic lactones. CYDECTIN Injectable is specially formulated to allow moxidectin to be absorbed from the site of injection and distributed internally to the areas of the body affected by endo- and/or ectoparasitism. Moxidectin binds selectively and with high affinity to glutamate-gated chloride ion channels which are critical to the function of invertebrate nerve and muscle cells. This interferes with neurotransmission resulting in paralysis and elimination of the parasite.

INDICATIONS

CYDECTIN Injectable, when administered at the recommended dose level of 0.2 mg/2.2 lb (0.2 mg/kg) body weight, is effective in the treatment and control of the following internal and external parasites of cattle:

Gastrointestinal Roundworms | Lungworms
Ostertagia ostertagi - Adults and L4(including inhibited Larvae) | Dictyocaulus viviparus - Adults and L4
Haemonchus placei - Adults | Cattle Grubs
Trichostrongylus axei - Adults and L4 | Hypoderma bovis
Trichostrongylus colubriformis - Adults and L4 | Hypoderma lineatum
Cooperia oncophora - Adults | Mites
Cooperia pectinata - Adults | Psoroptes ovis
Cooperia punctata - Adults and L4 | (Psoroptes communis var. bovis)
Cooperia spatulata - Adults | Lice
Cooperia surnabada - Adults and L4 | Linognathus vituli
Nematodirus helvetianus - Adults | Solenopotes capillatus
Oesophagostomum radiatum -
Adults and L4; Trichuris spp. - Adults

Persistent Activity: CYDECTIN Injectable has been proven to effectively protect cattle from reinfection with Dictyocaulus viviparus and Oesophagostomum radiatum for 42 days after treatment, Haemonchus placei for 35 days after treatment, and Ostertagia ostertagi and Trichostrongylus axei for 14 days after treatment.

Management Considerations for External Parasites: For most effective external parasite control, CYDECTIN Injectable should be administered to all cattle in the herd. Cattle entering the herd following this administration should be treated prior to introduction. Consult your veterinarian or a livestock entomologist for the most appropriate time to administer CYDECTIN Injectable in your location to effectively control external parasites.

DOSAGE

The recommended rate of administration for CYDECTIN Injectable is 1 mL for each 110 lb (50 kg) body weight to provide 0.2 mg moxidectin/2.2 lb (0.2 mg/kg) body weight. The table below will assist in the calculation of the appropriate volume of injectable which must be administered based on the weight of animal being treated. Be careful not to overdose animals; estimate animal’s body weight as closely as possible or weigh animals individually.

Weight (lb) | 165 | 220 | 330 | 440 | 550 | 660 | 770 | 880 | 990 | 1100
Weight (kg) | 75 | 100 | 150 | 200 | 250 | 300 | 350 | 400 | 450 | 500
Dose (mL) | 1.5 | 2.0 | 3.0 | 4.0 | 5.0 | 6.0 | 7.0 | 8.0 | 9.0 | 10.0

- Do not underdose. Ensure each animal receives a complete dose based on a current body weight. Underdosing may result in ineffective treatment, and encourage the development of parasite resistance.

ADMINISTRATION

CYDECTIN Injectable should be administered by subcutaneous injection under the loose skin in front of or behind the shoulder (Figure 1). Needles 1/2 to 3/4 inch in length and 16 to 18 gauge are recommended for subcutaneous injections. Use sterile, dry equipment and aseptic procedures when withdrawing and administering CYDECTIN.

Figure 1. Sites for administration of CYDECTIN Injectable

HUMAN WARNINGS

Not For Use in Humans. Keep this and all drugs out of the reach of children. For product questions, to report adverse reactions, or for a copy of the Safety Data Sheet (SDS), call Elanco Product & Veterinary Support at 1-800-428-4441.

RESIDUE WARNINGS

Cattle must not be slaughtered for human consumption within 21 days of treatment. This drug product is not approved for use in female dairy cattle 20 months of age or older, including dry dairy cows. Use in these cattle may cause drug residues in milk and/or in calves born to these cows. A withdrawal period has not been established for preruminating calves. Do not use in calves to be processed for veal.

ANIMAL SAFETY WARNINGS

Do not use in sick, debilitated, or underweight animals. In foreign countries there have been reports of adverse effects, including death. This product should not be used in calves less than 8 weeks of age because safety testing has not been done in the U.S. in calves less than 8 weeks of age.

ENVIRONMENTAL WARNINGS

Studies indicate that when moxidectin comes in contact with the soil, it readily and tightly binds to the soil and becomes inactive. Free moxidectin may adversely affect fish and certain aquatic organisms. Do not contaminate water by direct application or by improper disposal of drug containers.

OTHER WARNINGS

- Parasite resistance may develop to any dewormer, and has been reported for most classes of dewormers.
- Treatment with a dewormer used in conjunction with parasite management practices appropriate to the geographic area and the animal(s) to be treated may slow the development of parasite resistance.
- Fecal examinations or other diagnostic tests and parasite management history should be used to determine if the product is appropriate for the herd/flock, prior to the use of any dewormer. Following the use of any dewormer, effectiveness of treatment should be monitored (for example, with the use of a fecal egg count reduction test or another appropriate method).
- A decrease in a drug’s effectiveness over time as calculated by fecal egg count reduction tests may indicate the development of resistance to the dewormer administered. Your parasite management plan should be adjusted accordingly based on regular monitoring.

PRECAUTIONS

CYDECTIN Injectable has been formulated specifically for subcutaneous injection in cattle and should not be given by other routes of administration. Subcutaneous injection can cause transient local tissue reaction that may result in trim loss of edible tissue at slaughter if animals are slaughtered within 35 days after treatment. This product should not be used in other animal species as severe adverse reactions, including fatalities in dogs, may result.

CYDECTIN Injectable is effective against the migrating stage of cattle grubs (Hypoderma larvae). Treatment with CYDECTIN Injectable during the period when grubs are migrating through vital areas may cause undesirable host-parasite reactions. Killing H. lineatum when they are located in peri-esophageal tissues may cause bloat. Killing H. bovis when they are in the vertebral canal may cause staggering or hindlimb paralysis. Cattle should be treated as soon as possible after heel fly (warble fly) season to avoid this potential problem. Cattle treated with CYDECTIN Injectable at the end of fly season can be retreated during the winter without danger of grub-related reactions. Consult your veterinarian for more information regarding these secondary grub reactions and the correct time to treat with CYDECTIN Injectable.

ANIMAL SAFETY

U.S. tolerance and toxicity studies have demonstrated that CYDECTIN Injectable has an adequate margin of safety for use in cattle 8 weeks of age and older. No toxic signs were seen in growing cattle given up to 5 times the recommended dose. Calves as young as 8 weeks of age showed no toxic signs when treated with up to 3 times the recommended dose while nursing from cows concurrently treated with the recommended dose level of CYDECTIN Injectable. Mild, transient ataxia was noted in growing cattle receiving 10 times the recommended dose and in bulls treated at 4.5 times the recommended dose. In breeding animals (bulls and cows in estrous and during early, mid and late pregnancy), treatment with at least 3 times the recommended dose had no effect on breeding performance.

Signs of toxicity include ataxia, excessive salivation, depression, and mydriasis. These signs usually occur within 12 to 48 hours post-treatment.

STORAGE

Store product at or below 77°F (25°C). Protect from light. Use contents within 12 months of first puncture.

DISPOSAL

Do not contaminate water by direct application or by improper disposal of drug containers. Dispose of containers in an approved landfill or by incineration.

PACKAGE INFORMATION

CYDECTIN Injectable is available in 500 mL amber glass bottles.

Restricted Drug (CA) - Use Only As Directed.

Patent information at http://www.elancopatents.com

Manufactured for:
Elanco US Inc.
Greenfield, IN 46140 U.S.A

Made in China
Made in Italy

Cydectin, Elanco and the diagonal bar logo are trademarks of Elanco or its affiliates.
© 2023 Elanco or its affiliates.

Revised: September 2023

YL600406A
YL600406B

Elanco

Principal Display Panel - 500 mL Bottle Label

Elanco™

CYDECTINTM

moxidectin

Injectable Solution for Beef
and Nonlactating Dairy Cattle

Antiparasitic

Sterile

Contains 10 mg moxidectin/mL (5,000 mg/500 mL)

Not for use in female dairy cattle 20 months of age
or older (including dry dairy cows), veal calves,
and calves less than 8 weeks of age.

For Treatment of Infections and
Infestations Due to Internal
and External Parasites
of Cattle.

Contents 500 mL
(16.91 oz)

Approved by FDA under NADA# 141-220.